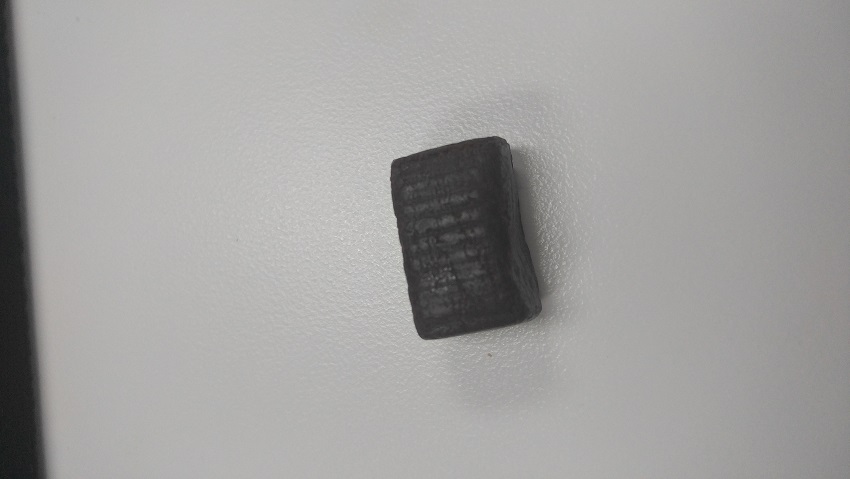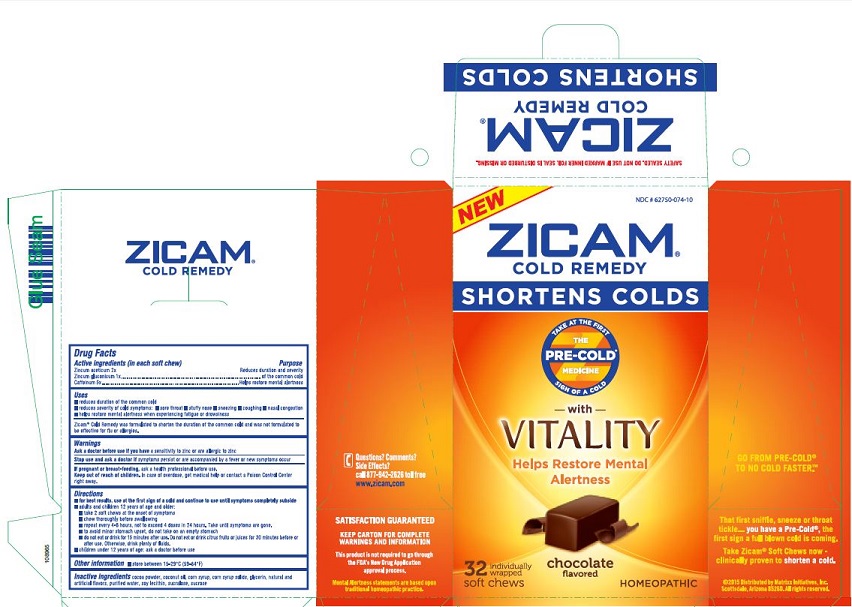 DRUG LABEL: Zicam Cold Remedy Soft Chews
NDC: 52642-232 | Form: TABLET, CHEWABLE
Manufacturer: BestCo Inc.
Category: homeopathic | Type: HUMAN OTC DRUG LABEL
Date: 20160224

ACTIVE INGREDIENTS: ZINC ACETATE 3.53 mg/1 1; CAFFEINE 0.03 mg/1 1; ZINC GLUCONATE 4.47 mg/1 1
INACTIVE INGREDIENTS: SUCROSE

Zincum aceticum 2X
Zincum gluconicum 1X
Caffeinum 5X

Active ingredients (in each soft chew)

Zincum aceticum 2X

Zincum gluconicum 1X

Caffeinum 5X

Purpose

Reduces duration and severity of the common cold

Helps restore mental alertness

Uses

- reduces duration of the common cold
- reduces severity of cold symptoms: sore throat, stuffy nose, sneezing, coughing, nasal congestion
- helps restore mental alertness when experiencing fatigue or drowsiness

WARNINGS

Zicam Cold Remedy was formulated to shorten the duration of the common cold and was not formulated to be effective for flu or allergies.

Ask a doctor before use if you have a sensitivity to zinc or are allergic to zinc

Stop use and ask a doctor if symptoms persist or are accompanied by a fever or new symptoms occur

PREGNANCY OR BREAST FEEDING

If pregnant or breast-feeding, ask a health professional before use.

Keep out of reach of children.

OVERDOSAGE

In case of overdose, get medical help or contact a Poison Control Center right away.

Directions

- for best results, use at the first sign of a cold and continue to use until to use until symptoms completely subside
- adults and children 12 years of age and older:
- take 2 soft chews at the onset of symptoms
- chew thoroughly before swallowing
- repeat every 2-6 hours, not to exceed 4 doses in 24 hours. Take until symptoms are gone.
- to avoid minor stomach upset, do not take on any empty stomach
- do not eat or drink for 15 minutes after use. Do not eat or drink citrus fruits or juices for 30 minutes before or after use. Otherwise, drink plenty of fluids.
- children under 12 years of age: ask a doctor before use.

Other information

- store between 15-29C (59-84F)

Inactive ingredients

cocoa powder, coconut oil, corn syrup, corn syrup solids, glycerin, natural and artificial flavors, purified water, soy lecithin, sucralose, sucrose